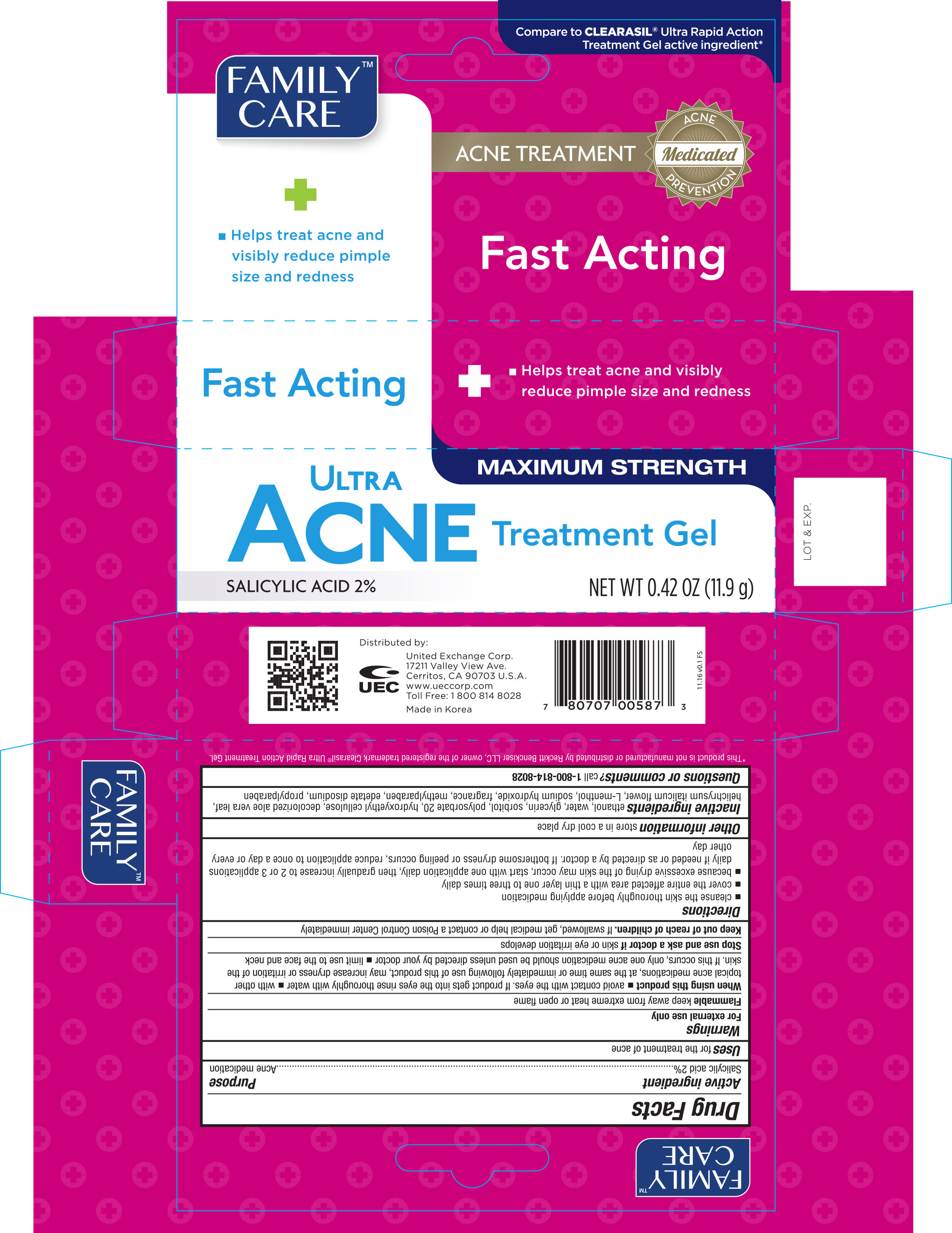 DRUG LABEL: Family Care Ultra Acne Treatment
NDC: 65923-587 | Form: GEL
Manufacturer: United Exchange Corp.
Category: otc | Type: HUMAN OTC DRUG LABEL
Date: 20170217

ACTIVE INGREDIENTS: SALICYLIC ACID 2 g/100 g
INACTIVE INGREDIENTS: ALCOHOL; WATER; GLYCERIN; SORBITOL; POLYSORBATE 20; ALOE VERA LEAF; HELICHRYSUM ITALICUM FLOWER; MENTHOL; SODIUM HYDROXIDE; METHYLPARABEN; EDETATE DISODIUM; PROPYLPARABEN

Active ingredient Purpose

Salicylic acid 2%.........................................................Acne medication

Uses

for the treatment of acne

Warnings

For external use only

Flammable keep away from extreme heat or open flame

When using this product

- avoid contact with the eyes. If product gets into the eyse rinse thoroughly with water
- with other topical acne medications, at the same time or immediately following use of this product, may increase dryness or irritation of the skin. If this occurs, only one acne medication should be used unless directed by your doctor
- limit use to the face and neck

Stop use and ask a doctor if skin or eye irritation develops

Keep out of reach of children. If swallowed, get medical help or contact a Poison Control Center immediately

Directions

- cleanse the skin thoroughly before applying medication
- cover the entire affected area with a thin layer one to three times daily
- because excessive drying of the skin may occur, start with one application daily, then gradually increase to 2 or 3 applications daily if needed

or as directed by a doctor. If bothersome dryness or peeling occurs, reduce application to once a dy or every other day

STORAGE AND HANDLING

Other informatiom

store in a cool dry place

INACTIVE INGREDIENT

Inactive ingredients ethanol, water, glycerin, sorbitol, polysorbate 20, hydroxyethyl cellulose, decolorized alove vera leaf, helichrysum italicum flover, L-menthol, sodium hydroxide, fragrance, methylparaben, edetate disodium, propylparaben

DOSAGE AND ADMINISTRATION

Distributed by:

United Exchange Corp.

17211 Valley View Ave.

Cerritos, CA 90703 U.S.A.

www.ueccorp.com

Made in Korea